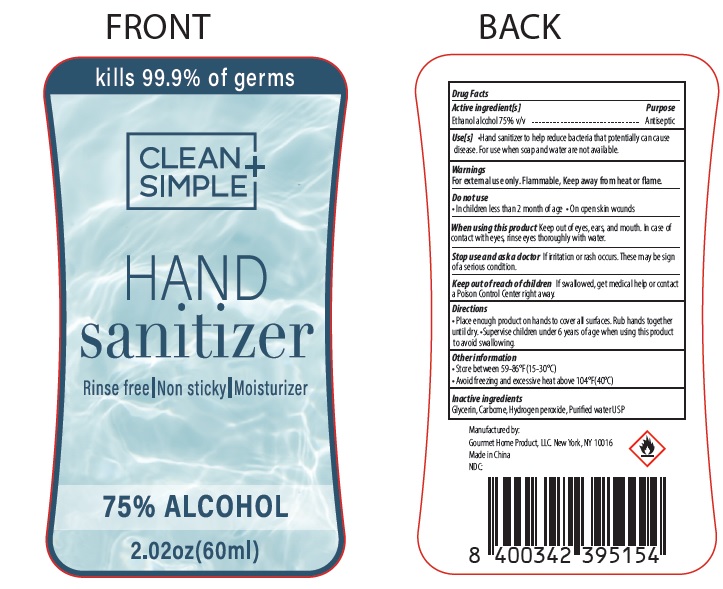 DRUG LABEL: Clean Simple Hand Sanitizer
NDC: 73928-003 | Form: LIQUID
Manufacturer: KINGKEY MBC LIFE TECHNOLOGY GROUP CO., LTD
Category: otc | Type: HUMAN OTC DRUG LABEL
Date: 20251007

ACTIVE INGREDIENTS: ALCOHOL 75 mL/100 mL
INACTIVE INGREDIENTS: GLYCERIN; AMINOMETHYLPROPANOL; CARBOMER 940; WATER

Clean Simple Hand Sanitizer

Active Ingredient

Alcohol 75%

Purpose

Antiseptic

Warnings

For external use only. Flammable. Keep away from heat or flame.

Do not use

- in children less than 2 months of age
- on open skin wounds

when using this product

- keep out of eyes, ears, and mouth.
- In case of contact with eyes, rinse eyes thoroughly with water.

stop use and ask a doctorif irritation or rash occurs. These may be signs of a serious condition.

Uses

- Hand Sanitizer to help reduce bacteria that potentially can cause disease.
- For use when soap and water are not available.

Directions

- Place enough product on hands to cover all surfaces. Rub hands together until dry.
- Supervise children under 6 years of age when using this product to avoid swallowing.

Keep out of reach of children

If swallowed, get medical help or contact a Poison Control Center right away

Other informatio

- Store between 15-30°C (59-86F)
- Avoid freezingandexcessive heatabove 40°C(104F)

Inactive Ingredient

Water, Glycerin, Carbomer, Aminomehtyl Propanol